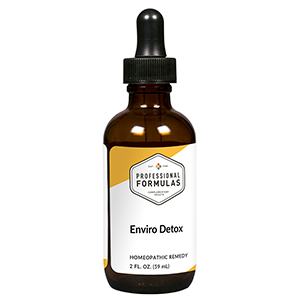 DRUG LABEL: Enviro Detox
NDC: 63083-6009 | Form: LIQUID
Manufacturer: Professional Complementary Health Formulas
Category: homeopathic | Type: HUMAN OTC DRUG LABEL
Date: 20190815

ACTIVE INGREDIENTS: ARCTIUM LAPPA ROOT OIL 3 [hp_X]/59 mL; TARAXACUM OFFICINALE 3 [hp_X]/59 mL; TRIFOLIUM PRATENSE FLOWER 3 [hp_X]/59 mL; CHLOROPHYLL 6 [hp_X]/59 mL; BENZENE 12 [hp_X]/59 mL; NAPHTHALENE 12 [hp_X]/59 mL; LIQUID PETROLEUM 12 [hp_X]/59 mL; SULFURIC ACID 12 [hp_X]/59 mL; LEAD 20 [hp_X]/59 mL; AIR 30 [hp_X]/59 mL; POLYCYCLIC AROMATIC HYDROCARBONS 30 [hp_X]/59 mL; AMMONIA 30 [hp_X]/59 mL
INACTIVE INGREDIENTS: ALCOHOL; WATER

X9

ACTIVE INGREDIENTS

Arctium lappa 3X
Taraxacum officinale 3X
Trifolium pratense 3X
Chlorophyll 6X
Benzinum 12X
Naphthalinum 12X
Petroleum 12X, 30X, 60X, 100X
Sulphuricum acidum 12X, 30X, 60X, 100X
Plumbum metallicum 20X, 30X, 60X
and all the following at 30X, 60X, 100X:
Air pollution
Various hydrocarbons
Water pollution

QUESTIONS

Professional Formulas

PO Box 2034 Lake Oswego, OR 97035

INDICATIONS

For the temporary relief of cough, shortness of breath, dry or sore throat, occasional headache, nausea, fatigue, or weakness due to sensitivity to or exposure to air or water pollutants.*

PURPOSE

*Claims based on traditional homeopathic practice, not accepted medical evidence. Not FDA evaluated.

WARNINGS

In case of overdose, get medical help or contact a poison control center right away.

Keep out of the reach of children.

PREGNANCY OR BREAST FEEDING

If pregnant or breastfeeding, ask a healthcare professional before use.

DIRECTIONS

Place drops under tongue 30 minutes before/after meals. Adults and children 12 years and over: Take 10 drops up to 3 times per day. Consult a physician for use in children under 12 years of age.

OTHER INFORMATION

Tamper resistant. If seal is broken, do not use. After opening, close container tightly and store at room temperature away from heat.

INACTIVE INGREDIENTS

20% ethanol, purified water.

LABEL

Est 1985

Professional Formulas

Complementary Health

Enviro Detox

Homeopathic Remedy

2 FL. OZ. (59 mL)